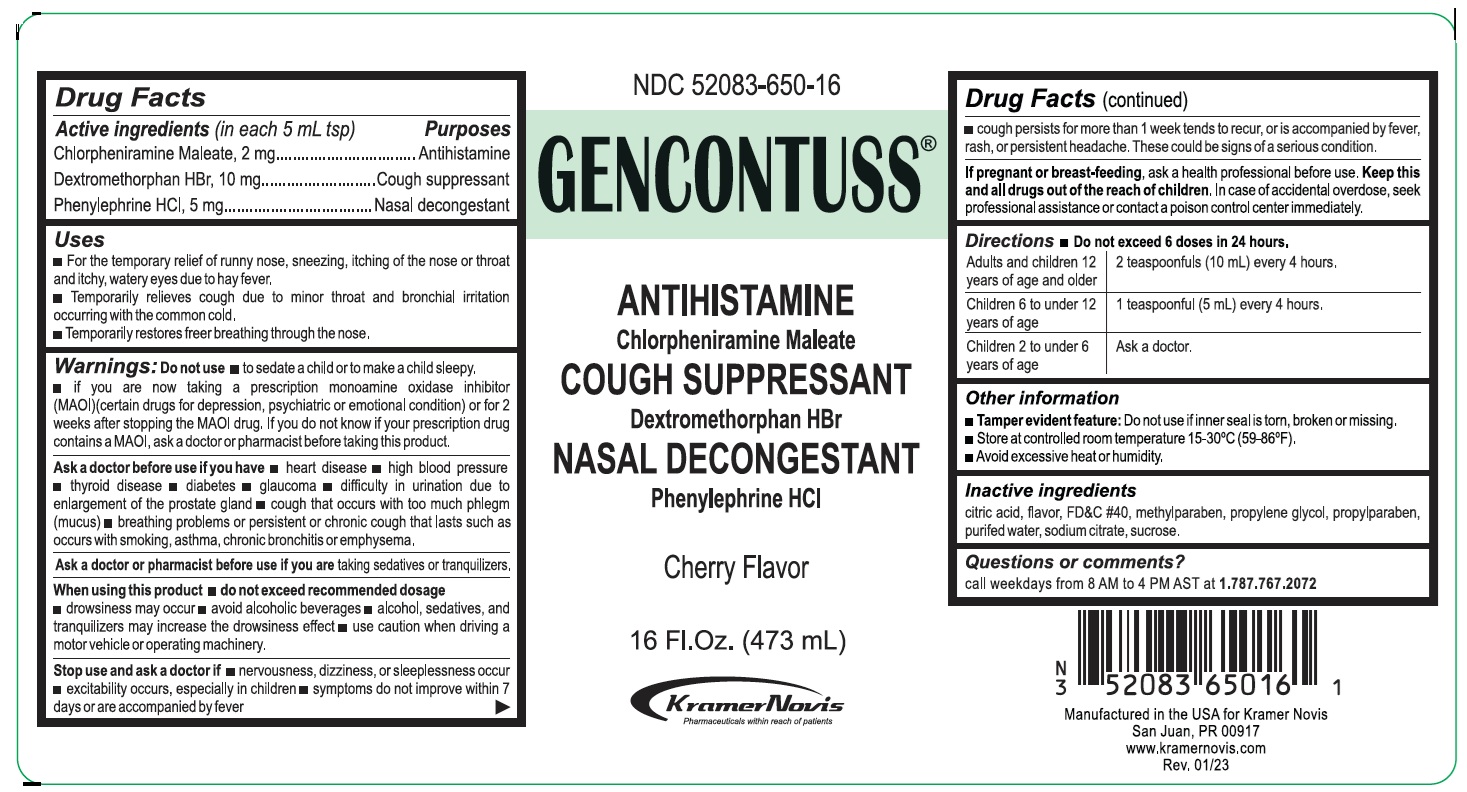 DRUG LABEL: GENCONTUSS
NDC: 52083-650 | Form: SOLUTION
Manufacturer: KRAMER NOVIS
Category: otc | Type: HUMAN OTC DRUG LABEL
Date: 20251204

ACTIVE INGREDIENTS: CHLORPHENIRAMINE MALEATE 2 mg/5 mL; DEXTROMETHORPHAN HYDROBROMIDE 10 mg/5 mL; PHENYLEPHRINE HYDROCHLORIDE 5 mg/5 mL
INACTIVE INGREDIENTS: CITRIC ACID MONOHYDRATE; FD&C RED NO. 40; METHYLPARABEN; PROPYLENE GLYCOL; PROPYLPARABEN; WATER; SODIUM CITRATE, UNSPECIFIED FORM; SUCROSE

GENCONTUSS®

Active ingredients (in each 5mL tsp)

Chlorpheniramine Maleate, 2 mg
Dextromethorphan HBr, 10 mg
Phenylephrine HCl, 5 mg

Purposes

Antihistamine
Cough suppressant
Nasal decongestant

Uses

• For the temporary relief of runny nose, sneezing, itching of the nose or throat and itchy, watery eyes due to hay fever.
• Temporarily relieves cough due to minor throat and bronchial irritation occurring with the common cold.
• Temporarily restores freer breathing through the nose.

Warnings:

Do not use • to sedate a child or to make a child sleepy.
• If you are now taking a prescription monoamine oxidase inhibitor (MAOI)(certain drugs for depression, psychiatric or emotional condition) or for 2 weeks after stopping the MAOI drug. If you do not know if your prescription drug contains a MAOI, ask a doctor or pharmacist before taking this product.

Ask a doctor before use if you have • heart disease • high blood pressure • thyroid disease • diabetes • glaucoma • difficulty in urination due to enlargement of the prostate gland • cough that occurs with too much phlegm (mucus) • breathing problems or persistent or chronic cough that lasts such as occurs with smoking, asthma, chronic bronchitis or emphysema.

Ask a doctor or pharmacist before use if you are taking sedatives or tranquilizers

When using this product • do not exceed recommended dosage• drowsiness may occur • avoid alcoholic beverages • alcohol, sedatives and tranquilizers may increase the drowsiness effect • use caution when driving a motor vehicle or operating machinery.

Stop use and ask a doctor if • nervousness, dizziness, or sleeplessness occur • excitability occurs, especially in children • symptoms do not improve within 7 days or are accompanied by fever • cough persists for more than 1 week tends to recur, or is accompanied by fever, rash, or persistent headache. These could be signs of a serious condition.

If pregnant or breast-feeding, ask a health professional before use.

KEEP OUT OF REACH OF CHILDREN

Keep this and all drugs out of the reach of children. In case of accidental overdose, seek professional assistance or contact a poison control center immediately.

Directions

• Do not exceed 6 doses in 24 hours.

Adults and children 12 years of age and older | 2 teaspoonfuls (10 mL) every 4 hours.
Children 6 to under 12 years of age | 1 teaspoonful (5 mL) every 4 hours.
Children 2 to under 6 years of age | Ask a doctor.

Other information

• Tamper evident feature: Do not use if inner seal is torn, broken or missing.
• Store at controlled room temperature 15-30⁰C(59-86⁰F).
• Avoid excessive heat or humidity.

Inactive Ingredients

citric acid, flavor, FD&C #40, methylparaben, propylene glycol, propylparaben, purified water, sodium citrate, sucrose.

Questions or comments?

call weekdays from 8 AM to 4 PM AST at 1.787.767.2072

ANTIHISTAMINE
Chlorpheniramine Maleate

COUGH SUPPRESSANT
Dextromethorphan Hbr

NASAL DECONGESTANT
Phenylephrine Hcl

Cherry Flavor

Kramer Novis
Pharmaceuticals within reach of patients

Manufactured in the USA for Kramer Novis
San Juan, PR 00917
www.kramernovis.com